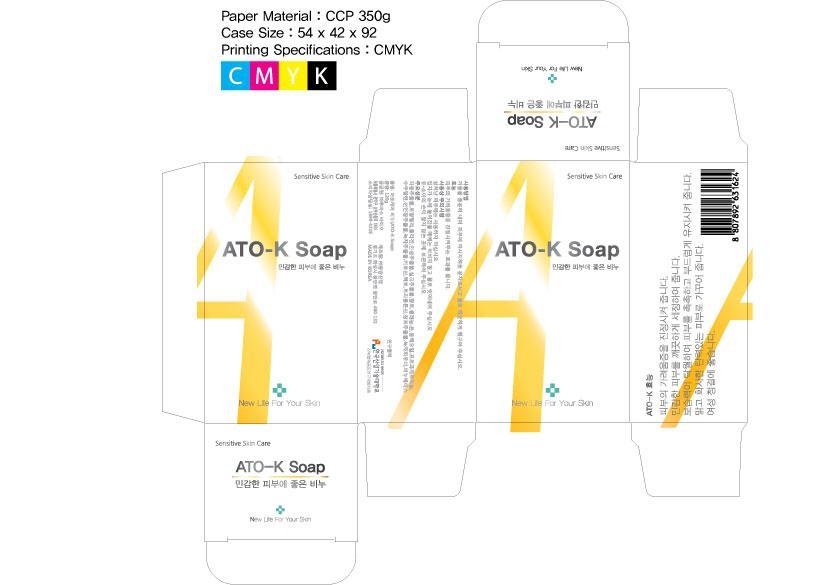 DRUG LABEL: ATO-K
NDC: 61165-2001 | Form: SOAP
Manufacturer: LUBASBIO CO., LTD 
Category: otc | Type: HUMAN OTC DRUG LABEL
Date: 20131123

ACTIVE INGREDIENTS: PANAX GINSENG ROOT OIL 0.5 g/100 g
INACTIVE INGREDIENTS: SODIUM PALMATE; CITRUS PARADISI FRUIT OIL

Drug Facts

ACTIVE INGREDIENT

panax ginseng root extract

INACTIVE INGREDIENT

sodium palmate, perfurm, illite, grapefruit extract, squalane, silver, collagen, honey, royal jelly, camellia sinensis leaf powder, silk ext, chitosan, camellia sinensis leaf ext, selenium aspartate, acorus calamus root ext, germanium dioxide, tricalosan, camellia japonica seed oil

PURPOSE

for sensitive skin care

keep out or reach of the children

INDICATIONS AND USAGE

apply 1 to 3 times with water and wash away

WARNINGS

do not swallow

DOSAGE AND ADMINISTRATION

for topical use only